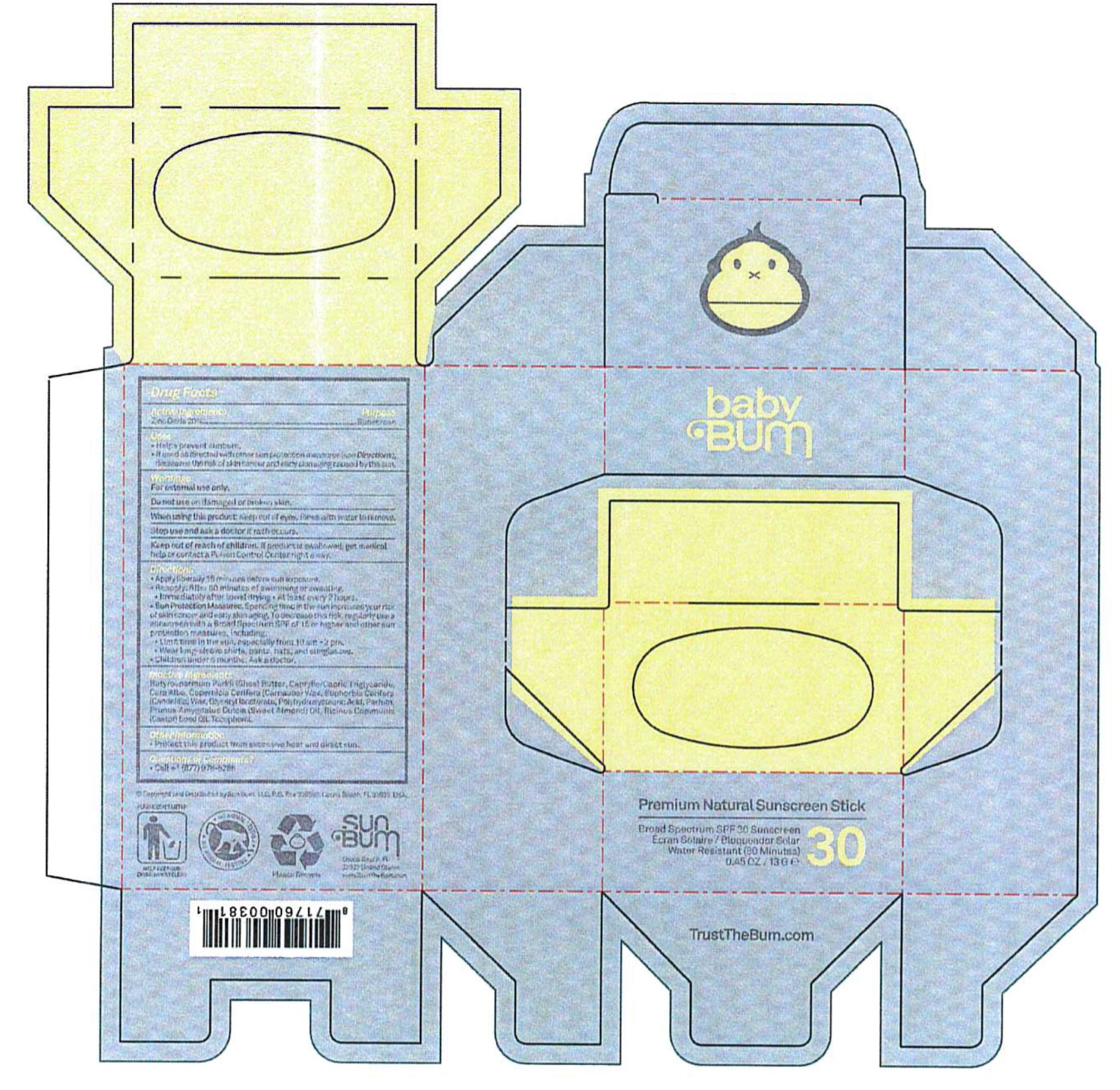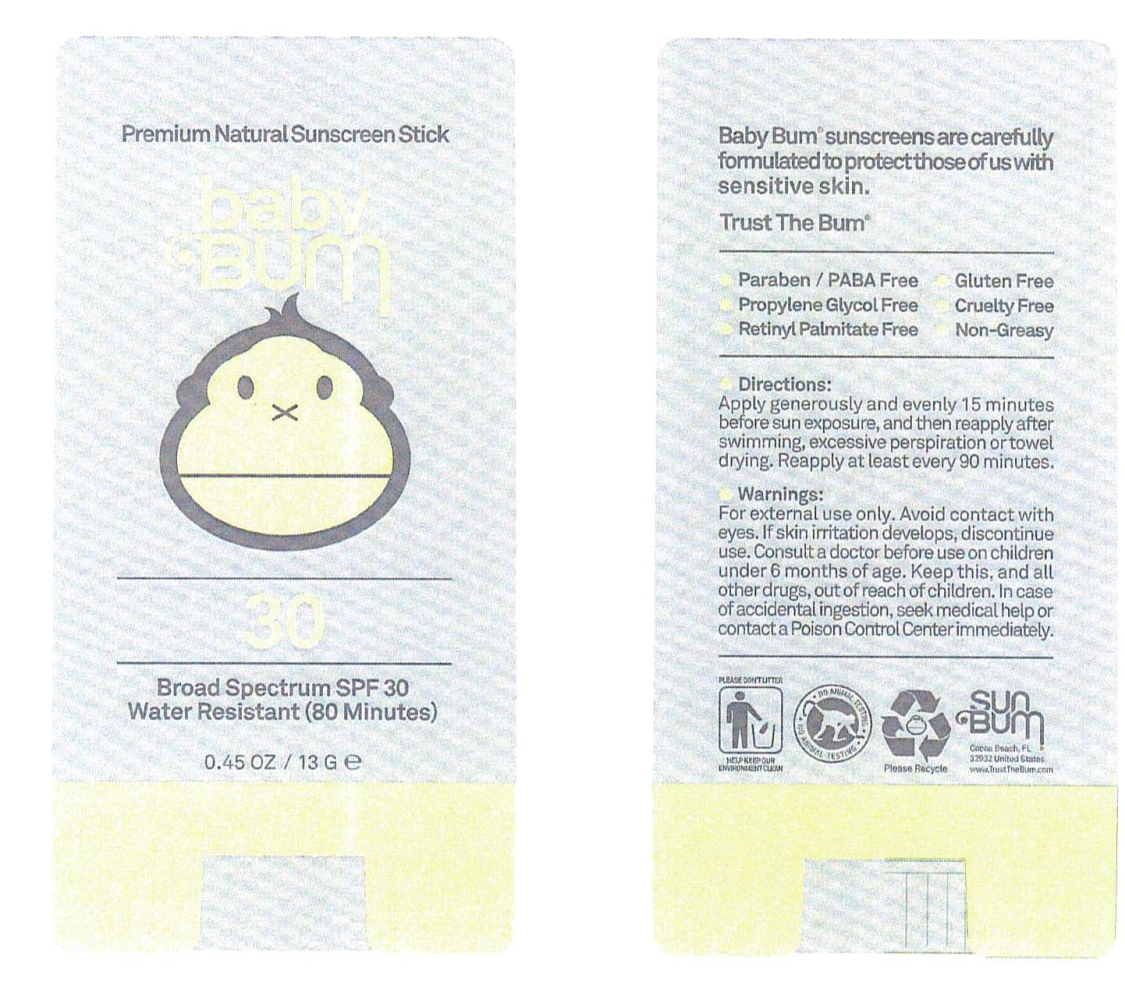 DRUG LABEL: Premium Natural Sunscreen Broad Spectrum SPF 30
NDC: 70157-007 | Form: STICK
Manufacturer: Baxter Laberatories
Category: otc | Type: HUMAN OTC DRUG LABEL
Date: 20170105

ACTIVE INGREDIENTS: ZINC OXIDE 20 g/100 g
INACTIVE INGREDIENTS: SHEANUT OIL; MEDIUM-CHAIN TRIGLYCERIDES; WHITE WAX; CARNAUBA WAX; CANDELILLA WAX; GLYCERYL ISOSTEARATE; POLYHYDROXYSTEARIC ACID (2300 MW); ALMOND OIL; CASTOR OIL; TOCOPHEROL

Baby Bum Premium Natural Sunscreen Stick Broad Spectrum SPF 30

Active Ingredients Purpose

Zinc Oxide 20% ........... Sunscreen

Uses

- Helps prevent sunburn
- If used as directed with other sun protection measures (see Directions), decreases the risk of skin cancer and early skin aging caused by the sun

Keep out of reach of children. If product is swallowed, get medical help or contact a Poison Control Center right away.

INDICATIONS AND USAGE

Stop used and ask a doctor if rash occurs

Warnings

For external use only

Do not use on damaged or broken skin

When using this Product: Keep out of eyes. Rinse with water to remove

Directions

- Apply liberally 15 minutes before sun exposure
- Reapply: After 80 minutes of swimming or sweating
- Immediately after towel drying
- At least every2 hours
- Sun Protection Measures. Spending time in the sun increases your risk of skin cancer and early skin aging. To decrease this risk, regularly use a sunscreen with a Broad Spectrum SPF of 15 or higher and other sun protection measures, including:
- Limit time in the sun, especially form 10 am - 2 pm.
- Wear long-sleeve shirts, pants, hats, and sunglasses
- Children under 6 months: Ask a doctor

Inactive Ingredients

Butyrospermum Parkii (shea) Butter, Caprylic/Capric Triglyceride, Cera Alba, Copernicia Cerifer(Carnauba) Wax, Euphorbia Cerifera (Candelilla) Wax, Blyceryl Isostearate, Polyhydroxystearic Acid, Parfum, Prunus Amygdalus Dulcis (Sweet Almond) Oil, Ricinus Communis (Castor) Seed Oil, Tocopherol

PACKAGE LABEL

Premium Natural Sunscreen Stick

Baby Bum 30

Broad Spectrum SPF 30

Water Resistant (80minutes

.45 OZ / 13 G